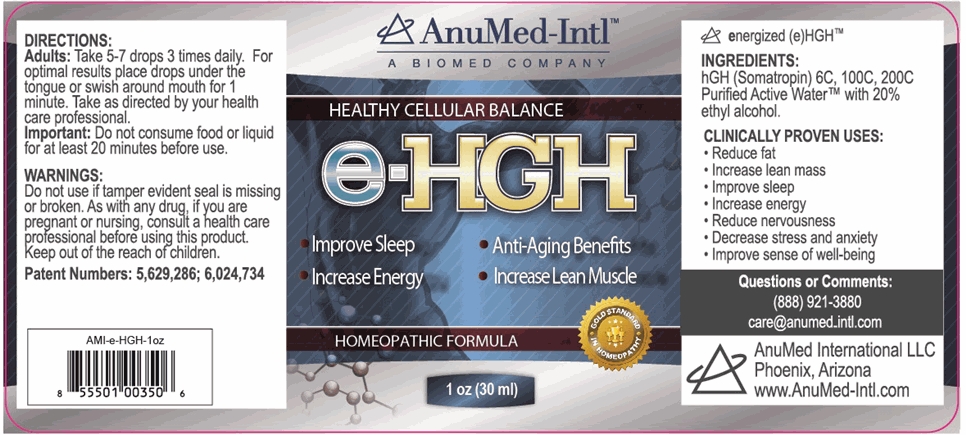 DRUG LABEL: e-HGH
NDC: 50970-002 | Form: LIQUID
Manufacturer: AnuMed International LLC
Category: homeopathic | Type: HUMAN OTC DRUG LABEL
Date: 20231129

ACTIVE INGREDIENTS: SOMATROPIN 6 [hp_C]/200 mL
INACTIVE INGREDIENTS: ALCOHOL; WATER

e-HGH
HEALTHY CELLULAR BALANCE
HOMEOPATHIC FORMULA

ACTIVE INGREDIENTS:

hGH (Somatropin) 6C, 100C, 200C

PURPOSE:

Improve Sleep, Increase Energy, Anti-Aging Benefits, Increase Lean Muscle

USES:

Reduce fat, Increase lean mass, Improve sleep, Increase energy, Reduce nervousness, Decrease stress and anxiety, Improve sense of well-being

WARNINGS:

Do Not Use

if tamper evident seal is missing or broken.

Pregnancy or Breast Feeding

As with any drug, it you are pregnant or nursing, consult a health care professional before using this product.

DIRECTIONS:

Adults:Take 5-7 drops 3 times daily. For optimal results place drops under the tongue or swish around mouth for 1 minute. Take as directed by your health care professional.

Important:Do not consume food or liquid for at least 20 minutes before use.

INACTIVE INGREDIENTS:

Purified Active WaterTMwith 20% ethyl alcohol.

QUESTIONS OR COMMENTS

(888) 921-3880

care@anumed-intl.com

Patent Numbers: 5,629,286; 6,024,734

Anumed International LLC
Phoenix Arizona
www.AnuMed-Intl.com

PACKAGE/LABEL PRINCIPAL DISPLAY PANEL

AnuMed Intl™

A Biomed Company

HEALTHY CELLULAR BALANCE

e-HGH

•Improve Sleep •Anti-Aging Benefits

•Increase Energy •Increase Lean Muscle

HOMEOPATHIC FORMULA

Gold Standard in Homeopathy

1 oz (30 ml)